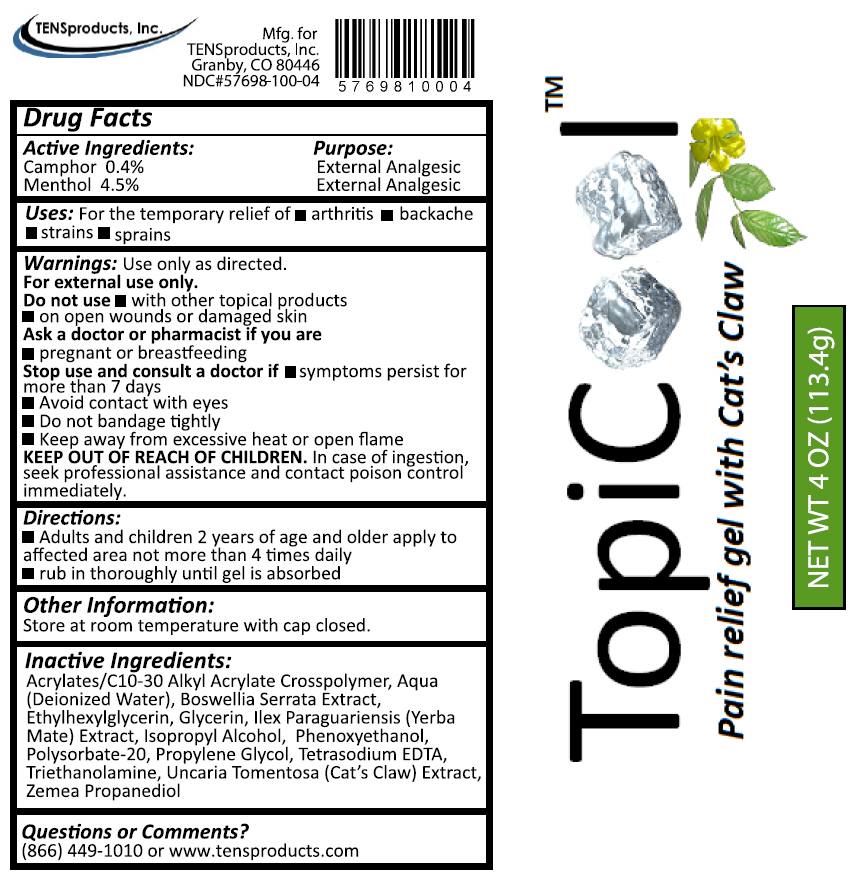 DRUG LABEL: TopiCool Pain Relief
NDC: 57698-100 | Form: GEL
Manufacturer: TENSproducts, Inc.
Category: otc | Type: HUMAN OTC DRUG LABEL
Date: 20181101

ACTIVE INGREDIENTS: MENTHOL, UNSPECIFIED FORM 4.5 g/100 g; CAMPHOR (NATURAL) 0.4 g/100 g
INACTIVE INGREDIENTS: CARBOMER COPOLYMER TYPE A (ALLYL PENTAERYTHRITOL CROSSLINKED); WATER; INDIAN FRANKINCENSE; ETHYLHEXYLGLYCERIN; GLYCERIN; ILEX PARAGUARIENSIS LEAF; ISOPROPYL ALCOHOL; PHENOXYETHANOL; POLYSORBATE 20; PROPYLENE GLYCOL; EDETATE SODIUM; TROLAMINE; CAT'S CLAW; TRIMETHYLOLPROPANE

TOPICOOL PAIN RELIEF GEL WITH CATS CLAW - Drug Facts

Active Ingredients:

Camphor 0.4%

Menthol 4.5%

Purpose:

External Analgesic

External Analgesic

Uses:

For the temporary relief of

- arthritis
- backache
- sprains
- strains

Warnings:

Use only as directed.
For external use only.

Do not use

- with other topical products
- on open wounds or damaged skin

Ask a doctor or pharmacist if you are

pregnant or breastfeeding

Stop use and consult a doctor if

symptoms persist for more than 7 days

GENERAL PRECAUTIONS

Avoid contact with eyes
Do not bandage tightly
Keep away from excessive heat or open flame

KEEP OUT OF REACH OF CHILDREN.

In case of ingestion, seek professional assistance and contact poison control immediately.

Directions:

- Adults and children 2 years of age and older apply to affected area not more than 4 times daily
- rub in thoroughly until gel is absorbed

Other information:

Store at room temperature with cap closed.

Inactive Ingredients

Acrylates/C10-30 Alkyl Acrylate Crosspolymer, Aqua (Deionized Water), Boswellia Serrata Extract, Ethylhexylglycerin, Glycerin, Ilex Paraguariensis (Yerba Mate) Extract, Isopropyl Alcohol, Phenoxyethanol, Polysorbate-20, Propylene Glycol, Tetrasodium EDTA, Triethanolamine, Uncaria Tomentosa (Cat's Claw) Extract, Zemea Propanediol

Questions or Comments?

(866) 449-1010 or www.tensproducts.com

PRINCIPAL DISPLAY PANEL - 113.4 g Tube Label

TopiCool™
Pain relief gel with Cat's Claw

NET WT 4 OZ (113.4g)